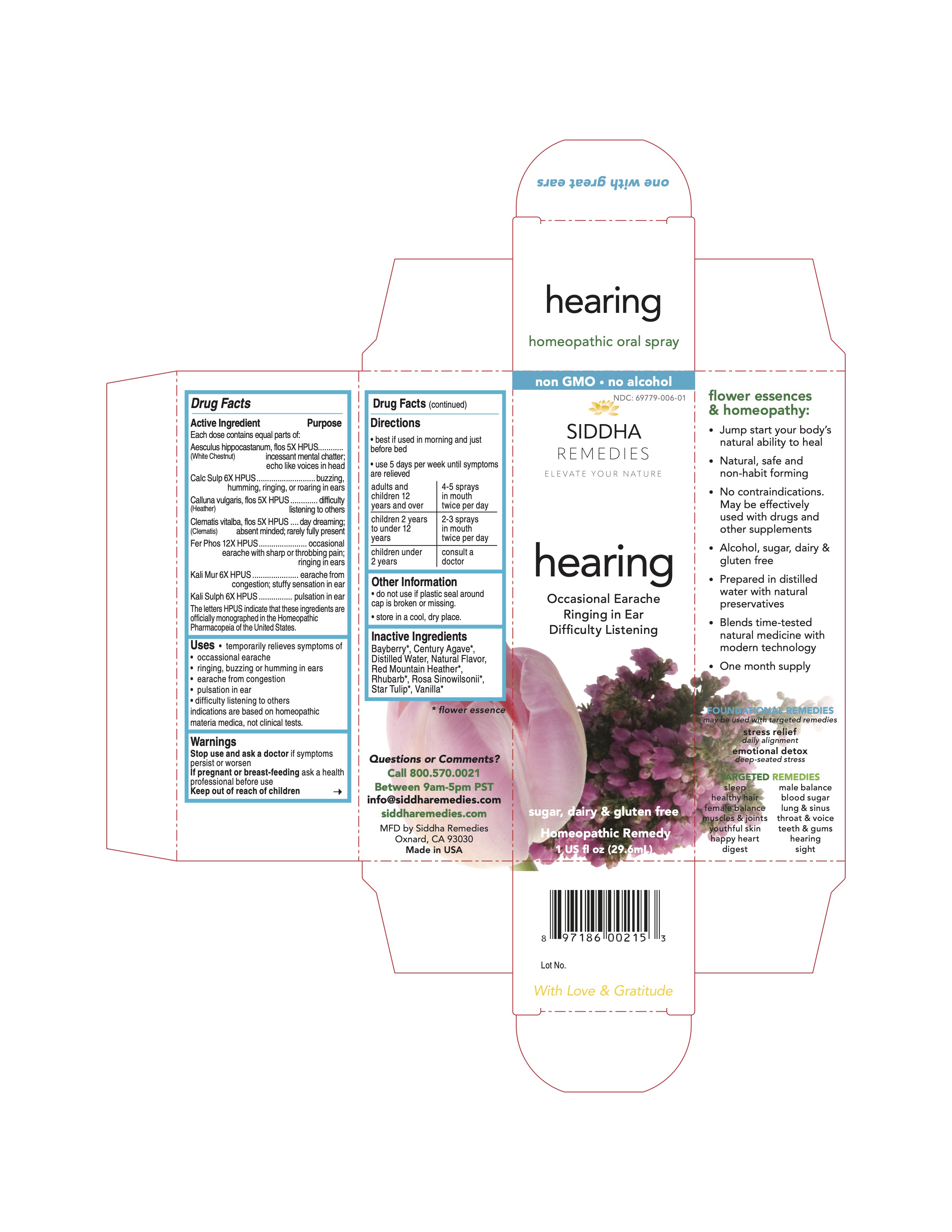 DRUG LABEL: hearing
NDC: 69779-006 | Form: SPRAY
Manufacturer: Siddha Flower Essences LLC
Category: homeopathic | Type: HUMAN OTC DRUG LABEL
Date: 20251231

ACTIVE INGREDIENTS: AESCULUS HIPPOCASTANUM FLOWER 5 [hp_X]/29.6 mL; CALCIUM SULFATE ANHYDROUS 6 [hp_X]/29.6 mL; CALLUNA VULGARIS FLOWERING TOP 5 [hp_X]/29.6 mL; CLEMATIS VITALBA FLOWER 5 [hp_X]/29.6 mL; FERROSOFERRIC PHOSPHATE 12 [hp_X]/29.6 mL; POTASSIUM CHLORIDE 6 [hp_X]/29.6 mL; POTASSIUM SULFATE 6 [hp_X]/29.6 mL
INACTIVE INGREDIENTS: WATER; RHUBARB; VANILLA

Drug Facts

Active Ingredient

Each dose contains equal parts of:
Aesculus hippocastanum, flos (White Chestnut) 5X HPUS
Calc Sulp 6X HPUS
Calluna vulgaris, flos (Heather) 5X HPUS
Clematis vitalba, flos (Clematis) 5X HPUS
Fer Phos 12X HPUS
Kali Mur 6X HPUS
Kali Sulph 6X HPUS

Purpose

Each dose contains equal parts of:
Aesculus hippocastanum, flos (White Chestnut) 5X HPUS..............incessant mental chatter, echo like voices in head
Calc Sulp 6X HPUS.....................................................................buzzing, humming, ringing, or roaring in ears
Calluna vulgaris, flos (Heather) 5X HPUS......................................difficulty listening to others
Clematis vitalba, flos (Clematis) 5X HPUS.....................................day dreaming; absent minded; rarely fully present
Fer Phos 12X HPUS....................................................................occasional earache with sharp or throbbing pain; ringing in ears
Kali Mur 6X HPUS.......................................................................earache from congestion; stuffy sensation in ear
Kali Sulph 6X HPUS....................................................................pulsation in ear

The letters HPUS indicate that these ingredients are officially monographed in the Homeopathic Pharmacopoeia of the United States.

Uses

- temporarily relieves symptoms of
- occasional earache
- ringing, buzzing or humming in ears
- earache from congestion
- pulsation in ear
- difficulty listening to others

indications are based on homeopathic materia medica, not clinical tests.

Warnings

Stop use and ask a doctor if symptoms persist or worsen

PREGNANCY OR BREAST FEEDING

If pregnant or breast-feeding ask a health professional before use

Keep out of reach of children

Directions

- best if used in morning and just before bed
- use 5 days per week until symptoms are relieved

adults and children 12 years and over | 4-5 sprays in mouth twice per day
children 2 years to under 12 years | 2-3 sprays in mouth twice per day
children under2 years | consult a doctor

Other Information

- do not use if plastic seal around cap is broken or missing.
- store in a cool, dry place.

Inactive Ingredients

Bayberry*, Century Agave*, Natural Flavor, Purified Water, Red Mountain Heather*, Rhubarb*, Rosa Sinowilsonii*, Star Tulip*, Vanilla*

*flower essence

DESCRIPTION

Comments or Questions?

Call 800.570.0021
Between 9am-5pm PST
info@siddhaflowers.com
siddhaflowers.com

MFD by Siddha Flower Essences
Oxnard, CA 93030

Made in USA

Side Panel

flower essences and homeopathy:

- Jump start your body's natural ability to heal
- Natural, safe and non-habit forming
- No contraindications. May be effectively used with drugs and other supplements
- Alcohol, sugar, dairy and gluten free
- Prepared in purified water with natural preservatives
- Blends time-tested natural medicine with modern technology
- One month supply

FOUNDATIONAL REMEDIES
may be used with targeted remedies

stress relief
daily alignment
emotional detox
deep-seated stress

TARGETED REMEDIES

sleep male balance
healthy hair blood sugar
female balance lung and sinus
muscles and joints throat and voice
youthful skin teeth and gums
happy heart hearing
digest sight

Principal Display Panel

non GMO - no alcohol
siddha cell salts + flower essences
hearing
Occasional Earache
Ringing in Ear
Difficulty Listening
sugar, dairy and gluten free
Homeopathic Remedy
1 US fl oz (29.6mL)